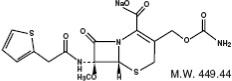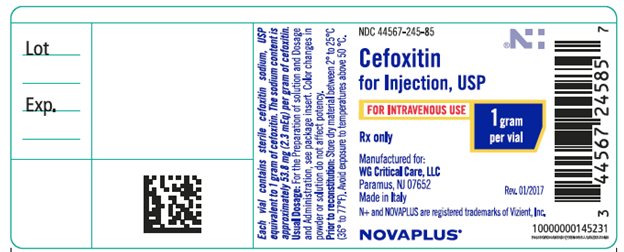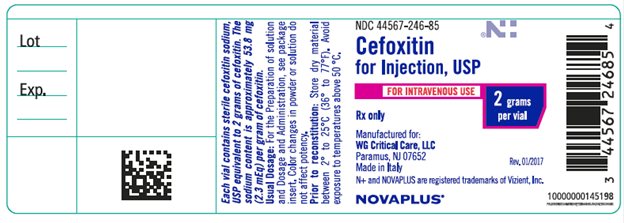 DRUG LABEL: Cefoxitin
NDC: 44567-245 | Form: INJECTION, POWDER, FOR SOLUTION
Manufacturer: WG Critical Care, LLC
Category: prescription | Type: HUMAN PRESCRIPTION DRUG LABEL
Date: 20251112

ACTIVE INGREDIENTS: CEFOXITIN SODIUM 1 g/1 1

Cefoxitin for Injection, USP

Rx only

To reduce the development of drug-resistant bacteria and maintain the effectiveness of Cefoxitin for Injection and other antibacterial drugs, Cefoxitin for Injection should be used only to treat or prevent infections that are proven or strongly suspected to be caused by bacteria.

DESCRIPTION

Cefoxitin for Injection, USP contains cefoxitin sodium a semi-synthetic, broad-spectrum cephalosporin antibiotic for parenteral administration. It is derived from cephalosporin C, which is produced by Cephalosporium Acremonium. It is the sodium salt of 3-(hydroxymethyl)-7-methoxy-8-oxo-7-[2-(2-thienyl)acetamido]-5-thia-1-azabicyclo[4.2.0]oct-2-ene-2-carboxylate carbamate (ester).

The molecular formula is C16H16N3NaO7S2, and the structural formula is:

Cefoxitin for Injection, USP contains approximately 53.8 mg (2.3 milliequivalents) of sodium per gram of cefoxitin activity. Solutions of Cefoxitin for Injection, USP range from colorless to light amber in color. The pH of freshly constituted solutions usually ranges from 4.2 to 7.0.

Each conventional vial contains sterile cefoxitin sodium, USP equivalent to 1 or 2 g cefoxitin.

CLINICAL PHARMACOLOGY

Following an intravenous dose of 1 gram, serum concentrations were 110 mcg/mL at 5 minutes, declining to less than 1 mcg/mL at 4 hours. The half-life after an intravenous dose is 41 to 59 minutes. Approximately 85 percent of cefoxitin is excreted unchanged by the kidneys over a 6-hour period, resulting in high urinary concentrations. Probenecid slows tubular excretion and produces higher serum levels and increases the duration of measurable serum concentrations.

Cefoxitin passes into pleural and joint fluids and is detectable in antibacterial concentrations in bile.

In a published study of geriatric patients ranging in age from 64 to 88 years with normal renal function for their age (creatinine clearance ranging from 31.5 to 174.0 mL/min), the half-life for cefoxitin ranged from 51 to 90 minutes, resulting in higher plasma concentrations than in younger adults. These changes were attributed to decreased renal function associated with the aging process.

Microbiology

Mechanism of Action

Cefoxitin is a bactericidal agent that acts by inhibition of bacterial cell wall synthesis. Cefoxitin has activity in the presence of some beta-lactamases, both penicillinases and cephalosporinases, of Gram-negative and Gram-positive bacteria.

Mechanism of Resistance

Resistance to cefoxitin is primarily through hydrolysis by beta-lactamase, alteration of penicillin-binding proteins (PBPs), and decrease permeability.

Cefoxitin has been shown to be active against most isolates of the following bacteria, both in vitro and in clinical infections as described in the INDICATIONS AND USAGE section:

Gram-positive bacteria

Staphylococcus aureus (methicillin-susceptible isolates only)

Staphylococcus epidermidis (methicillin-susceptible isolates only)

Streptococcus agalactiae

Streptococcus pneumoniae

Streptococcus pyogenes

Gram-negative bacteria

Escherichia coli

Haemophilus influenzae

Klebsiella spp.

Morganella morganii

Neisseria gonorrhoeae

Proteus mirabilis

Proteus vulgaris

Providencia spp.

Anaerobic bacteria

Clostridium spp.

Peptococcus niger

Peptostreptococcus spp.

Bacteroides spp.

The following in vitro data are available, but their clinical significance is unknown. At least 90 percent of the following microorganisms exhibit an in vitro minimum inhibitory concentration (MIC) less than or equal to the susceptible breakpoint for cefoxitin. However, the efficacy of cefoxitin in treating clinical infections due to these microorganisms has not been established in adequate and well-controlled clinical trials.

Gram-negative bacteria

Eikenella corrodens (non-β-lactamase producers)

Anaerobic bacteria

Clostridium perfringens

Prevotella bivia

Susceptibility Testing

For specific information regarding susceptibility test interpretive criteria and associated test methods and quality control standards recognized by FDA for this drug, please see: https://www.fda.gov/STIC.

INDICATIONS AND USAGE

Treatment

Cefoxitin for Injection, USP is indicated for the treatment of serious infections caused by susceptible strains of the designated microorganisms in the diseases listed below.

(1) Lower respiratory tract infections, including pneumonia and lung abscess, caused by Streptococcus pneumoniae, other streptococci (excluding enterococci, e.g., Enterococcus faecalis [formerly Streptococcus faecalis]), Staphylococcus aureus (including penicillinase-producing strains), Escherichia coli, Klebsiella species, Haemophilus influenzae, and Bacteroides species.

(2) Urinary tract infections caused by Escherichia coli, Klebsiella species, Proteus mirabilis, Morganella morganii, Proteus vulgaris and Providencia species (including P. rettgeri).

(3) Intra-abdominal infections, including peritonitis and intra-abdominal abscess, caused by Escherichia coli, Klebsiella species, Bacteroides species including Bacteroides fragilis, and Clostridium species.

(4) Gynecological infections, including endometritis, pelvic cellulitis, and pelvic inflammatory disease caused by Escherichia coli, Neisseria gonorrhoeae (including penicillinase-producing strains), Bacteroides species including B. fragilis, Clostridium species, Peptococcus niger, Peptostreptococcus species, and Streptococcus agalactiae. Cefoxitin for Injection, USP, like cephalosporins, has no activity against Chlamydia trachomatis. Therefore, when Cefoxitin for Injection, USP is used in the treatment of patients with pelvic inflammatory disease and C. trachomatis is one of the suspected pathogens, appropriate anti-chlamydial coverage should be added.

(5) Septicemia caused by Streptococcus pneumoniae, Staphylococcus aureus (including penicillinase-producing strains), Escherichia coli, Klebsiella species, and Bacteroides species including B. fragilis.

(6) Bone and joint infections caused by Staphylococcus aureus (including penicillinase-producing strains).

(7) Skin and skin structure infections caused by Staphylococcus aureus (including penicillinase-producing strains), Staphylococcus epidermidis, Streptococcus pyogenes and other streptococci (excluding enterococci e.g., Enterococcus faecalis [formerly Streptococcus faecalis]), Escherichia coli, Proteus mirabilis, Klebsiella species, Bacteroides species including B. fragilis, Clostridium species, Peptococcus niger, and Peptostreptococcus species.

Appropriate culture and susceptibility studies should be performed to determine the susceptibility of the causative organisms to Cefoxitin for Injection, USP. Therapy may be started while awaiting the results of these studies.

In randomized comparative studies, Cefoxitin for Injection, USP and cephalothin were comparably safe and effective in the management of infections caused by gram-positive cocci and gram-negative rods susceptible to the cephalosporins. Cefoxitin for Injection, USP has a high degree of stability in the presence of bacterial beta-lactamases, both penicillinases and cephalosporinases.

Many infections caused by aerobic and anaerobic gram-negative bacteria resistant to some cephalosporins respond to Cefoxitin for Injection, USP. Similarly, many infections caused by aerobic and anaerobic bacteria resistant to some penicillin antibiotics (ampicillin, carbenicillin, penicillin G) respond to treatment with Cefoxitin for Injection, USP. Many infections caused by mixtures of susceptible aerobic and anaerobic bacteria respond to treatment with Cefoxitin for Injection, USP.

Prevention

Cefoxitin for Injection, USP is indicated for the prophylaxis of infection in patients undergoing uncontaminated gastrointestinal surgery, vaginal hysterectomy, abdominal hysterectomy, or cesarean section.

If there are signs of infection, specimens for culture should be obtained for identification of the causative organism so that appropriate treatment may be instituted.

To reduce the development of drug-resistant bacteria and maintain the effectiveness of Cefoxitin for Injection, USP and other antibacterial drugs, Cefoxitin for Injection, USP should be used only to treat or prevent infections that are proven or strongly suspected to be caused by susceptible bacteria. When culture and susceptibility information are available, they should be considered in selecting or modifying antibacterial therapy. In the absence of such data, local epidemiology and susceptibility patterns may contribute to the empiric selection of therapy.

CONTRAINDICATIONS

Cefoxitin for Injection is contraindicated in patients who have shown hypersensitivity to cefoxitin and the cephalosporin group of antibiotics.

WARNINGS

BEFORE THERAPY WITH CEFOXITIN FOR INJECTION IS INSTITUTED, CAREFUL INQUIRY SHOULD BE MADE TO DETERMINE WHETHER THE PATIENT HAS HAD PREVIOUS HYPERSENSITIVITY REACTIONS TO CEFOXITIN, CEPHALOSPORINS, PENICILLINS, OR OTHER DRUGS. THIS PRODUCT SHOULD BE GIVEN WITH CAUTION TO PENICILLIN-SENSITIVE PATIENTS. ANTIBIOTICS SHOULD BE ADMINISTERED WITH CAUTION TO ANY PATIENT WHO HAS DEMONSTRATED SOME FORM OF ALLERGY, PARTICULARLY TO DRUGS. IF AN ALLERGIC REACTION TO CEFOXITIN FOR INJECTION OCCURS, DISCONTINUE THE DRUG. SERIOUS HYPERSENSITIVITY REACTIONS MAY REQUIRE EPINEPHRINE AND OTHER EMERGENCY MEASURES.

Clostridium difficile associated diarrhea (CDAD) has been reported with the use of nearly all antibacterial agents, including cefoxitin, and may range in severity from mild diarrhea to fatal colitis. Treatment with antibacterial agents alters the normal flora of the colon leading to overgrowth of C. difficile.

C. difficile produces toxins A and B which contribute to the development of CDAD.

Hypertoxin producing strains of C. difficile cause increased morbidity and mortality, as these infections can be refractory to antimicrobial therapy and may require colectomy. CDAD must be considered in all patients who present with diarrhea following antibiotic use. Careful medical history is necessary since CDAD has been reported to occur over two months after the administration of antibacterial agents.

If CDAD is suspected or confirmed, ongoing antibiotic use not directed against C. difficile may need to be discontinued. Appropriate fluid and electrolyte management, protein supplementation, antibiotic treatment of C. difficile, and surgical evaluation should be instituted as clinically indicated.

PRECAUTIONS

General

The total daily dose should be reduced when Cefoxitin for Injection is administered to patients with transient or persistent reduction of urinary output due to renal insufficiency (see DOSAGE AND ADMINISTRATION), because high and prolonged serum antibiotic concentrations can occur in such individuals from usual doses.

Antibiotics (including cephalosporins) should be prescribed with caution in individuals with a history of gastrointestinal disease, particularly colitis.

As with other antibiotics, prolonged use of Cefoxitin for Injection may result in overgrowth of nonsusceptible organisms. Repeated evaluation of the patient’s condition is essential. If superinfection occurs during therapy, appropriate measures should be taken.

Prescribing Cefoxitin for Injection in the absence of a proven or strongly suspected bacterial infection or a prophylactic indication is unlikely to provide benefit to the patient and increases the risk of the development of drug-resistant bacteria.

Information for Patients

Patients should be counseled that antibacterial drugs including Cefoxitin for Injection should only be used to treat bacterial infections. They do not treat viral infections (e.g., the common cold). When Cefoxitin for Injection is prescribed to treat a bacterial infection, patients should be told that although it is common to feel better early in the course of therapy, the medication should be taken exactly as directed. Skipping doses or not completing the full course of therapy may (1) decrease the effectiveness of the immediate treatment and (2) increase the likelihood that bacteria will develop resistance and will not be treatable by Cefoxitin for Injection or other antibacterial drugs in the future.

Diarrhea is a common problem caused by antibiotics, which usually ends when the antibiotic is discontinued. Sometimes after starting the treatment with antibiotics, patients can develop watery and bloody stools (with or without stomach cramps and fever) even as late as two or more months after having taken the last dose of the antibiotic. If this occurs, patients should contact their physician as soon as possible.

Laboratory Tests

As with any potent antibacterial agent, periodic assessment of organ system functions, including renal, hepatic, and hematopoietic, is advisable during prolonged therapy.

Drug Interactions

Increased nephrotoxicity has been reported following concomitant administration of cephalosporins and aminoglycoside antibiotics.

Drug/Laboratory Test Interactions

As with cephalothin, high concentrations of cefoxitin (>100 mcg/mL) may interfere with measurement of serum and urine creatinine levels by the Jaffé reaction, and produce false increases of modest degree in the levels of creatinine reported. Serum samples from patients treated with cefoxitin should not be analyzed for creatinine if withdrawn within 2 hours of drug administration.

High concentrations of cefoxitin in the urine may interfere with measurement of urinary 17-hydroxy-corticosteroids by the Porter-Silber reaction, and produce false increases of modest degree in the levels reported.

A false-positive reaction for glucose in the urine may occur. This has been observed with CLINITEST† reagent tablets.

Carcinogenesis, Mutagenesis, Impairment of Fertility

Long-term studies in animals have not been performed with cefoxitin to evaluate carcinogenic or mutagenic potential. Studies in rats treated intravenously with 400 mg/kg of cefoxitin (approximately 3 times the maximum recommended human dose) revealed no effects on fertility or mating ability.

Pregnancy

Reproduction studies performed in rats and mice at parenteral doses of approximately one to seven and one-half times the maximum recommended human dose did not reveal teratogenic or fetal toxic effects, although a slight decrease in fetal weight was observed.

There are, however, no adequate and well-controlled studies in pregnant women. Because animal reproduction studies are not always predictive of human response, this drug should be used during pregnancy only if clearly needed.

In the rabbit, cefoxitin was associated with a high incidence of abortion and maternal death. This was not considered to be a teratogenic effect but an expected consequence of the rabbit’s unusual sensitivity to antibiotic-induced changes in the population of the microflora of the intestine.

Nursing Mothers

Cefoxitin is excreted in human milk in low concentrations. Caution should be exercised when Cefoxitin for Injection is administered to a nursing woman.

Pediatric Use

Safety and efficacy in pediatric patients from birth to 3 months of age have not yet been established. In pediatric patients 3 months of age and older, higher doses of Cefoxitin for Injection have been associated with an increased incidence of eosinophilia and elevated SGOT.

Geriatric Use

Of the 1,775 subjects who received cefoxitin in clinical studies, 424 (24%) were 65 and over, while 124 (7%) were 75 and over. No overall differences in safety or effectiveness were observed between these subjects and younger subjects, and other reported clinical experience has not identified differences in responses between the elderly and younger patients, but greater sensitivity of some older individuals cannot be ruled out (see CLINICAL PHARMACOLOGY).

This drug is known to be substantially excreted by the kidney, and the risk of toxic reactions to this drug may be greater in patients with impaired renal function. Because elderly patients are more likely to have decreased renal function, care should be taken in dose selection, and it may be useful to monitor renal function (see DOSAGE AND ADMINISTRATION and PRECAUTIONS).

ADVERSE REACTIONS

Cefoxitin for Injection is generally well tolerated. The most common adverse reactions have been local reactions following intravenous injection. Other adverse reactions have been encountered infrequently.

Local Reactions

Thrombophlebitis has occurred with intravenous administration.

Allergic Reactions

Rash (including exfoliative dermatitis and toxic epidermal necrolysis), urticaria, flushing, pruritus, eosinophilia, fever, dyspnea, and other allergic reactions including anaphylaxis, interstitial nephritis and angioedema have been noted.

Cardiovascular

Hypotension.

Gastrointestinal

Diarrhea, including documented pseudomembranous colitis which can appear during or after antibiotic treatment. Nausea and vomiting have been reported rarely.

Neuromuscular

Possible exacerbation of myasthenia gravis.

Blood

Eosinophilia, leukopenia including granulocytopenia, neutropenia, anemia, including hemolytic anemia, thrombocytopenia, and bone marrow depression. A positive direct Coombs test may develop in some individuals, especially those with azotemia.

Liver Function

Transient elevations in SGOT, SGPT, serum LDH, and serum alkaline phosphatase; and jaundice have been reported.

Renal Function

Elevations in serum creatinine and/or blood urea nitrogen levels have been observed. As with the cephalosporins, acute renal failure has been reported rarely. The role of Cefoxitin for Injection in changes in renal function tests is difficult to assess, since factors predisposing to prerenal azotemia or to impaired renal function usually have been present.

In addition to the adverse reactions listed above which have been observed in patients treated with Cefoxitin for Injection, the following adverse reactions and altered laboratory test results have been reported for cephalosporin class antibiotics:

Urticaria, erythema multiforme, Stevens-Johnson syndrome, serum sickness-like reactions, abdominal pain, colitis, renal dysfunction, toxic nephropathy, false-positive test for urinary glucose, hepatic dysfunction including cholestasis, elevated bilirubin, aplastic anemia, hemorrhage, prolonged prothrombin time, pancytopenia, agranulocytosis, superinfection, vaginitis including vaginal candidiasis.

Several cephalosporins have been implicated in triggering seizures, particularly in patients with renal impairment when the dosage was not reduced. (See DOSAGE AND ADMINISTRATION). If seizures associated with drug therapy occur, the drug should be discontinued. Anticonvulsant therapy can be given if clinically indicated.

To report SUSPECTED ADVERSE EVENTS, contact WG Critical Care, LLC at 1-866-562-4708 or FDA at 1-800-FDA-1088 or www.fda.gov.

OVERDOSAGE

The acute intravenous LD50 in the adult female mouse and rabbit was about 8 g/kg and greater than 1 g/kg, respectively. The acute intraperitoneal LD50 in the adult rat was greater than 10 g/kg.

DOSAGE AND ADMINISTRATION

Treatment

Adults

The usual adult dosage range is 1 gram to 2 grams every 6 to 8 hours. Dosage should be determined by susceptibility of the causative organisms, severity of infection, and the condition of the patient (see Table 1 for dosage guidelines).

If C. trachomatis is a suspected pathogen, appropriate anti-chlamydial coverage should be added, because cefoxitin sodium has no activity against this organism.

Cefoxitin for Injection may be used in patients with reduced renal function with the following dosage adjustments:

In adults with renal insufficiency, an initial loading dose of 1 gram to 2 grams may be given. After a loading dose, the recommendations for maintenance dosage (Table 2) may be used as a guide.

When only the serum creatinine level is available, the following formula (based on sex, weight, and age of the patient) may be used to convert this value into creatinine clearance. The serum creatinine should represent a steady state of renal function.

Males: | Weight (kg) x (140-age)
Males: | 72 x serum creatinine (mg/100 mL)

Females: 0.85 x above value

In patients undergoing hemodialysis, the loading dose of 1 gram to 2 grams should be given after each hemodialysis, and the maintenance dose should be given as indicated in Table 2.

Antibiotic therapy for group A beta-hemolytic streptococcal infections should be maintained for at least 10 days to guard against the risk of rheumatic fever or glomerulonephritis. In staphylococcal and other infections involving a collection of pus, surgical drainage should be carried out where indicated.

Pediatric Patients

The recommended dosage in pediatric patients 3 months of age and older is 80 to 160 mg/kg of body weight per day divided into four to six equal doses. The higher dosages should be used for more severe or serious infections. The total daily dosage should not exceed 12 grams.

At this time no recommendation is made for pediatric patients from birth to 3 months of age (see PRECAUTIONS).

In pediatric patients with renal insufficiency, the dosage and frequency of dosage should be modified consistent with the recommendations for adults (see Table 2).

Prevention

Effective prophylactic use depends on the time of administration. Cefoxitin for Injection usually should be given one-half to one hour before the operation, which is sufficient time to achieve effective levels in the wound during the procedure. Prophylactic administration should usually be stopped within 24 hours since continuing administration of any antibiotic increases the possibility of adverse reactions but, in the majority of surgical procedures, does not reduce the incidence of subsequent infection.

For prophylactic use in uncontaminated gastrointestinal surgery, vaginal hysterectomy, or abdominal hysterectomy, the following doses are recommended:

Adults:

2 grams administered intravenously just prior to surgery (approximately one-half to one hour before the initial incision) followed by 2 grams every 6 hours after the first dose for no more than 24 hours.

Pediatric Patients (3 months and older):

30 to 40 mg/kg doses may be given at the times designated above.

Cesarean Section Patients:

For patients undergoing cesarean section, either a single 2 gram dose administered intravenously as soon as the umbilical cord is clamped OR a 3-dose regimen consisting of 2 grams given intravenously as soon as the umbilical cord is clamped followed by 2 grams 4 and 8 hours after the initial dose is recommended. (See CLINICAL STUDIES.)

Table 1. Guidelines for Dosage of Cefoxitin for Injection

Type of Infection | Daily Dosage | Frequency and Route
Uncomplicated forms* of infections such as pneumonia, urinary tract infection, cutaneous infection | 3 to 4 grams | 1 gram every; 6 to 8 hours IV
Moderately severe or severe infections | 6 to 8 grams | 1 gram every 4 hours; or; 2 grams every 6 to 8 hours IV
Infections commonly needing antibiotics in higher dosage (e.g., gas gangrene) | 12 grams | 2 grams every 4 hours; or; 3 grams every 6 hours IV

*Including patients in whom bacteremia is absent or unlikely.

Table 2. Maintenance Dosage of Cefoxitin for Injection in Adults with Reduced Renal Function

Renal Function | Creatinine; Clearance (mL/min) | Dose (Grams) | Frequency
Mild impairment | 50 to 30 | 1 to 2 | Every 8 to 12 hours
Moderate impairment | 29 to 10 | 1 to 2 | Every 12 to 24 hours
Severe impairment | 9 to 5 | 0.5 to 1 | Every 12 to 24 hours
Essentially no function | < 5 | 0.5 to 1 | Every 24 to 48 hours

Table 3. Preparation of Solution for Intravenous Administration

Strength | Amount of Diluent to be Added (mL)** | Approximate Withdrawable Volume (mL) | Approximate; Average; Concentration (mg/mL)
1 gram Vial | 10 | 10.5 | 95
2 gram Vial | 10 or 20 | 11.1 or 21 | 180 or 95

**Shake to dissolve and let stand until clear.

Preparation of Solution

Table 3 is provided for convenience in constituting Cefoxitin for Injection for intravenous administration.

For Vials

One gram should be constituted with at least 10 mL, and 2 grams with 10 mL or 20 mL, of Sterile Water for Injection, Bacteriostatic Water for Injection, 0.9 percent Sodium Chloride Injection, or 5 percent Dextrose Injection. These primary solutions may be further diluted in 50 mL to 1000 mL of the diluents listed under the Vialsportion of the Compatibility and Stability section.

Benzyl alcohol as a preservative has been associated with toxicity in neonates. While toxicity has not been demonstrated in pediatric patients greater than 3 months of age, in whom use of Cefoxitin for Injection may be indicated, small pediatric patients in this age range may also be at risk for benzyl alcohol toxicity. Therefore, diluent containing benzyl alcohol should not be used when Cefoxitin for Injection is constituted for administration to pediatric patients in this age range.

Administration

Cefoxitin for Injection may be administered intravenously after constitution.

Parenteral drug products should be inspected visually for particulate matter and discoloration prior to administration whenever solution and container permit.

Intravenous Administration

The intravenous route is preferable for patients with bacteremia, bacterial septicemia, or other severe or life threatening infections, or for patients who may be poor risks because of lowered resistance resulting from such debilitating conditions as malnutrition, trauma, surgery, diabetes, heart failure, or malignancy, particularly if shock is present or impending.

For intermittent intravenous administration, a solution containing 1 gram or 2 grams in 10 mL of Sterile Water for Injection can be injected over a period of 3 to 5 minutes. Using an infusion system, it may also be given over a longer period of time through the tubing system by which the patient may be receiving other intravenous solutions. However, during infusion of the solution containing Cefoxitin for Injection, it is advisable to temporarily discontinue administration of any other solutions at the same site.

For the administration of higher doses by continuous intravenous infusion, a solution of Cefoxitin for Injection may be added to an intravenous bottle containing 5 percent Dextrose Injection, 0.9 percent Sodium Chloride Injection, or 5 percent Dextrose and 0.9 percent Sodium Chloride Injection. BUTTERFLY®†† or scalp vein-type needles are preferred for this type of infusion.

Solutions of Cefoxitin for Injection, like those of most beta-lactam antibiotics, should not be added to aminoglycoside solutions (e.g., gentamicin sulfate, tobramycin sulfate, amikacin sulfate) because of potential interaction. However, Cefoxitin for Injection and aminoglycosides may be administered separately to the same patient.

Compatibility and Stability

Vials

Cefoxitin for Injection, as supplied in vials and constituted to 1 gram/10 mL with Sterile Water for Injection, Bacteriostatic Water for Injection, (see Preparation of Solution), 0.9 percent Sodium Chloride Injection, or 5 percent Dextrose Injection, maintains satisfactory potency for 6 hours at room temperature or for one week under refrigeration (below 5ºC).

These primary solutions may be further diluted in 50 mL to 1000 mL of the following diluents and maintain potency for an additional 18 hours at room temperature or an additional 48 hours under refrigeration:

0.9 percent Sodium Chloride Injection
5 percent or 10 percent Dextrose Injection
5 percent Dextrose and 0.9 percent Sodium Chloride Injection
5 percent Dextrose Injection with 0.2 percent or 0.45 percent saline solution
Lactated Ringer’s Injection
5 percent Dextrose in Lactated Ringer’s Injection
5 percent Sodium Bicarbonate Injection
M/6 sodium lactate solution
Mannitol 5% and 10%

After the periods mentioned above, any unused solutions should be discarded.

HOW SUPPLIED

Cefoxitin for Injection, USP is a dry white to off-white powder supplied in conventional vials containing cefoxitin sodium as follows:

NDC 44567-245-85 | Cefoxitin for Injection, USP contains cefoxitin sodium equivalent to 1 gram cefoxitin (carton of 25 vials).
NDC 44567-246-85 | Cefoxitin for Injection, USP contains cefoxitin sodium equivalent to 2 grams cefoxitin (carton of 25 vials).

The container closure is not made with natural rubber latex.

Special storage instructions

Cefoxitin for Injection, USP in the dry state should be stored between 2º to 25ºC (36º to 77ºF). Avoid exposure to temperatures above 50ºC. The dry material as well as solutions tend to darken, depending on storage conditions; product potency, however, is not adversely affected.

CLINICAL STUDIES

A prospective, randomized, double-blind, placebo-controlled clinical trial was conducted to determine the efficacy of short-term prophylaxis with Cefoxitin for Injection in patients undergoing cesarean section who were at high risk for subsequent endometritis because of ruptured membranes. Patients were randomized to receive either three doses of placebo (n=58), a single dose of Cefoxitin for Injection (2 g) followed by two doses of placebo (n=64), or a three-dose regimen of Cefoxitin for Injection (each dose consisting of 2 g) (n=60), given intravenously, usually beginning at the time of clamping of the umbilical cord, with the second and third doses given 4 and 8 hours post-operatively. Endometritis occurred in 16/58 (27.6%) patients given placebo, 5/63 (7.9%) patients given a single dose of Cefoxitin for Injection, and 3/58 (5.2%) patients given three doses of Cefoxitin for Injection. The differences between the two groups treated with Cefoxitin for Injection and placebo with respect to endometritis were statistically significant (p<0.01) in favor of Cefoxitin for Injection. The differences between the one-dose and three-dose regimens of Cefoxitin for Injection were not statistically significant.

Two double-blind, randomized studies compared the efficacy of a single 2 gram intravenous dose of Cefoxitin for Injection to a single 2 gram intravenous dose of cefotetan in the prevention of surgical site-related infection (major morbidity) and non-site-related infections (minor morbidity) in patients following cesarean section. In the first study, 82/98 (83.7%) patients treated with Cefoxitin for Injection and 71/95 (74.7%) patients treated with cefotetan experienced no major or minor morbidity. The difference in the outcomes in this study (95% CI: -0.03, +0.21) was not statistically significant. In the second study, 65/75 (86.7%) patients treated with Cefoxitin for Injection and 62/76 (81.6%) patients treated with cefotetan experienced no major or minor morbidity. The difference in the outcomes in this study (95% Cl: -0.08, +0.18) was not statistically significant.

In clinical trials of patients with intra-abdominal infections due to Bacteroides fragilis group microorganisms, eradication rates at 1 to 2 weeks posttreatment for isolates were in the range of 70% to 80%. Eradication rates for individual species are listed below:

Bacteroides distasonis | 7/10 | (70%)
Bacteroides fragilis | 26/33 | (79%)
Bacteroides ovatus | 10/13 | (77%)
B. thetaiotaomicron | 13/18 | (72%)

NOTES:

†Clinitest is a trademark of Seimens Healthcare Diagnostics Inc.

††Registered trademark of Abbott Laboratories, Inc.

N+ and NOVAPLUS are registered trademarks of Vizient, Inc.

Manufactured for:

WG Critical Care, LLC

Paramus, NJ 07652

Made in Italy

Revised: March 2019

PRINCIPAL DISPLAY PANEL - 1 gram

NDC 44567-245-85

Cefoxitin for Injection, USP

1 gram per vial

For Intravenous Use

Rx only

PRINCIPAL DISPLAY PANEL - 2 gram

NDC 44567-246-85

Cefoxitin for Injection, USP

2 grams per vial

For Intravenous Use

Rx only